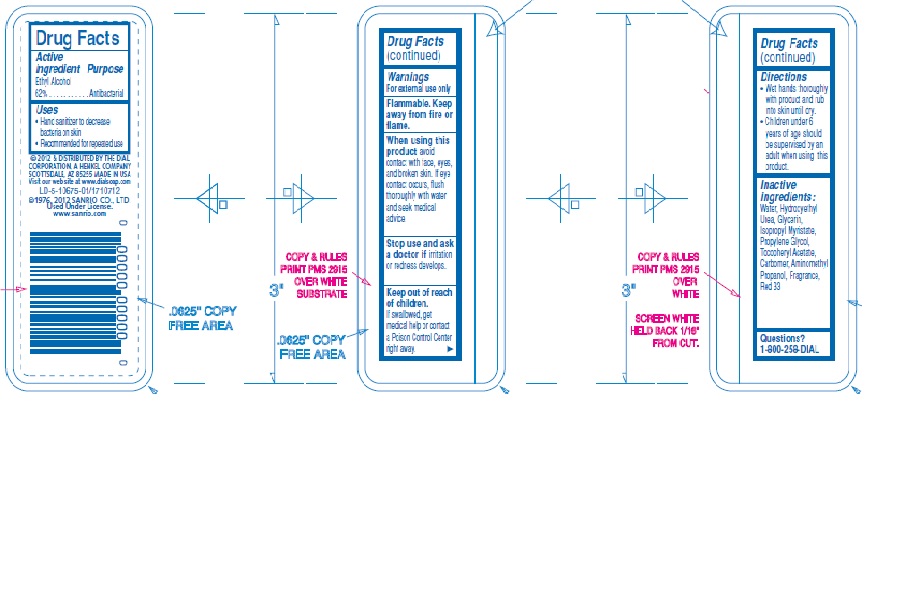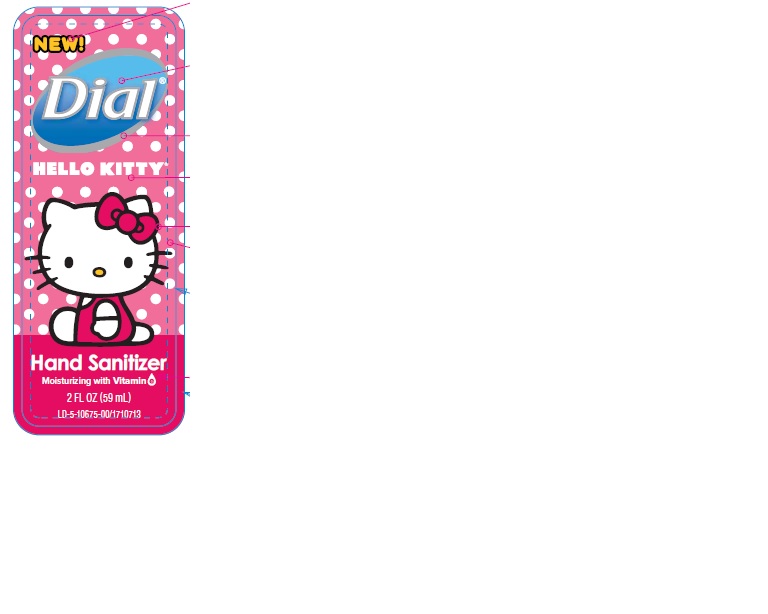 DRUG LABEL: Hello Kitty Hand Sanitizer
NDC: 54340-256 | Form: LIQUID
Manufacturer: The Dial Corporation, a Henkel company
Category: otc | Type: HUMAN OTC DRUG LABEL
Date: 20150803

ACTIVE INGREDIENTS: ALCOHOL 0.62 mL/1 mL
INACTIVE INGREDIENTS: WATER

ACTIVE INGREDIENT

Ethyl alcohol 62%

PURPOSE

Antibacterial

INDICATIONS AND USAGE

- Hand Sanitizer

WARNINGS

- For external use only
- Flammable. Keep away from fire or flame.

WHEN USING

avoid contact with face, eyes, and broken skin. If eye contact occurs, flush thoroughly with water and seek medical advice

Stop use and ask a doctor if irritation or redness develops.

KEEP OUT OF REACH OF CHILDREN

If swallowed, get medical help or contact a Poison Control Center right away.

INSTRUCTIONS FOR USE

Wet hands thoroughly with product and rub into skin until dry

Children under 6 years of age should be supervised by an adult when using this product.

INACTIVE INGREDIENT

Water (Aqua), Hydroxyethyl Urea, Glycerin, Isopropyl Myristate, Propylene Glycol, Tocopheryl Acetate, Carbomer, Aminomethyl Propanol, Fragrance (parfume), Red 33 (CI 17200)

QUESTIONS

1-800-258-3425

DOSAGE AND ADMINISTRATION

Topical liquid